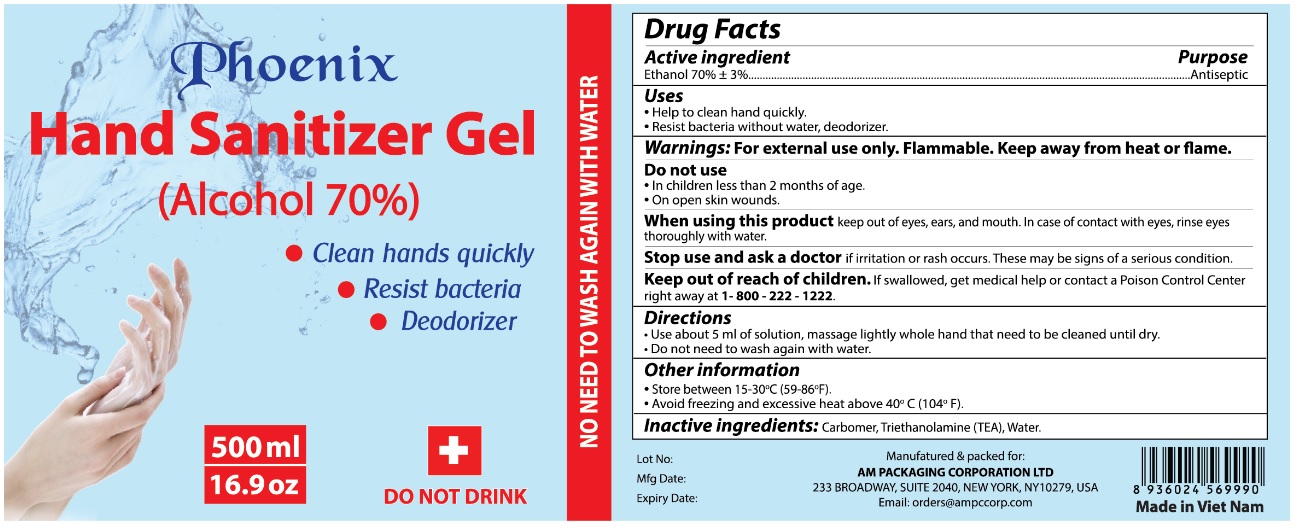 DRUG LABEL: Phoenix Hand Sanitizer Gel
NDC: 80666-555 | Form: GEL
Manufacturer: THANH CONG PHARMACEUTICAL AND TRADING CO.,LTD
Category: otc | Type: HUMAN OTC DRUG LABEL
Date: 20201005

ACTIVE INGREDIENTS: ALCOHOL 70 mL/100 mL
INACTIVE INGREDIENTS: CARBOMER HOMOPOLYMER, UNSPECIFIED TYPE; TROLAMINE; WATER

Phoenix Hand Sanitizer Gel

Active ingredient

Ethanol 70% + 3%

Purpose

Antiseptic

Uses

• Help to clean hand quickly.

• Resist bacteria without water, deodorizer.

WARNINGS

Warnings: For external use only. Flammable. Keep away from heat or flame.

Do not use

• In children less than 2 months of age.

• On open skin wounds.

When using this product keep out of eyes, ears and mouth. In case of contact with eyes, rinse eyes thoroughly with water.

Stop use and ask a doctor if irritation or rash occurs. These may be signs of a serious condition.

Keep out of reach of children. If swallowed, get medical help or contact a Poison Control Center right away at 1 - 800 -222 - 1222.

Directions

• Use about 5 ml of solution, massage lightly whole hand that need to be cleaned until dry.

• Do not need to wash again with water.

Other information

• Store between 15-30°C (59-86°F).

• Avoid freezing and excessive heat above 40°C (104°F).

Inactive ingredients: Carbomer, Triethanolamine (TEA), Water.

Alcohol 70%

• Clean hands quickly

• Resist bacteria

• Deodorizer

DO NOT DRINK

NO NEED TO WASH AGAIN WITH WATER

Manufactured & packed for:

AM PACKAGING CORPORATION LTD

233 BROADWAY, SUITE 2040, NEW YORK, NY 10279, USA

Email: orders@ampccorp.com

Made in Viet Nam